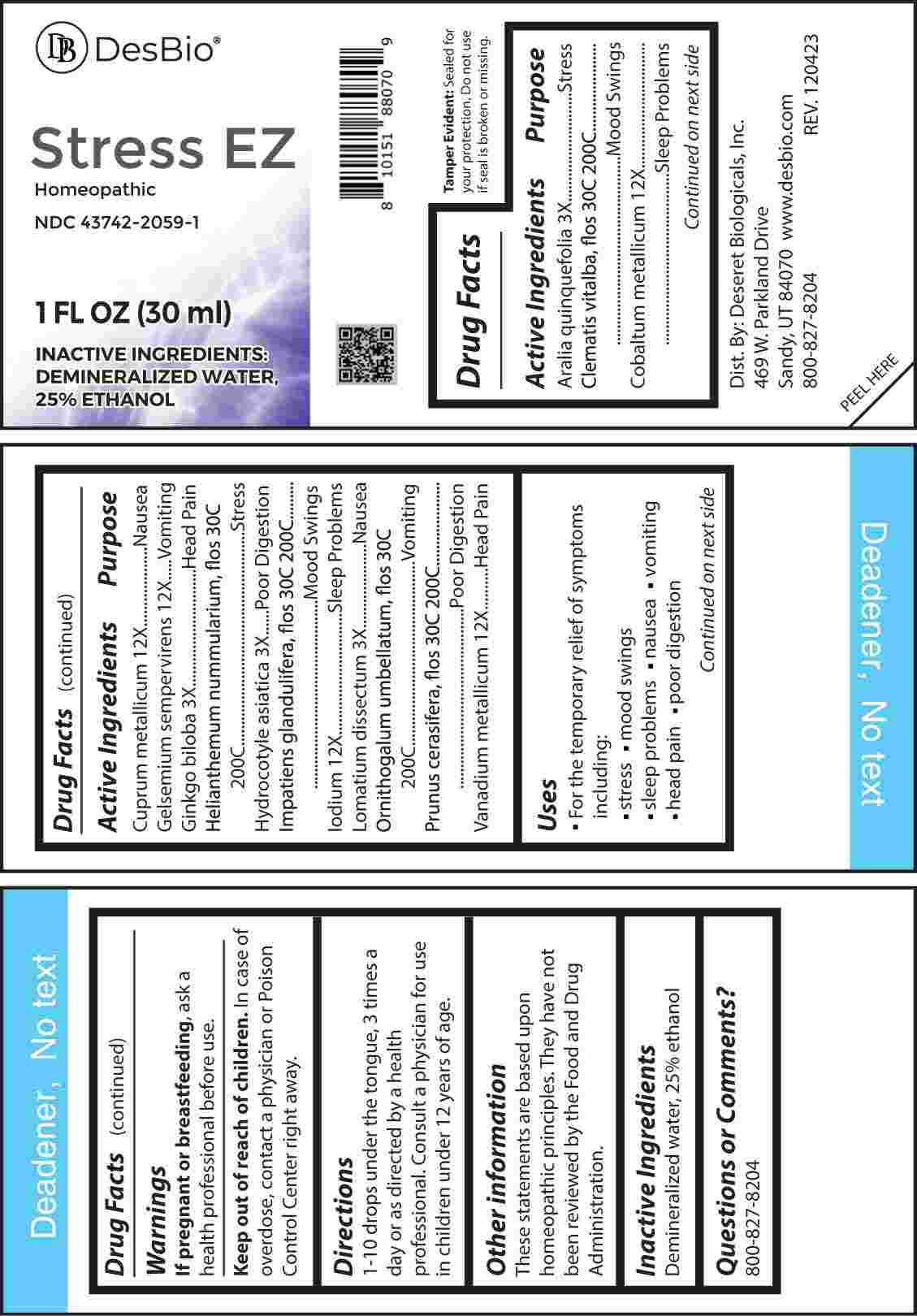 DRUG LABEL: Stress
NDC: 43742-2059 | Form: LIQUID
Manufacturer: Deseret Biologicals, Inc.
Category: homeopathic | Type: HUMAN OTC DRUG LABEL
Date: 20240313

ACTIVE INGREDIENTS: AMERICAN GINSENG 3 [hp_X]/1 mL; GINKGO 3 [hp_X]/1 mL; CENTELLA ASIATICA WHOLE 3 [hp_X]/1 mL; LOMATIUM DISSECTUM ROOT 3 [hp_X]/1 mL; COBALT 12 [hp_X]/1 mL; COPPER 12 [hp_X]/1 mL; GELSEMIUM SEMPERVIRENS ROOT 12 [hp_X]/1 mL; IODINE 12 [hp_X]/1 mL; VANADIUM 12 [hp_X]/1 mL; CLEMATIS VITALBA FLOWER 30 [hp_C]/1 mL; HELIANTHEMUM NUMMULARIUM FLOWER 30 [hp_C]/1 mL; IMPATIENS GLANDULIFERA FLOWER 30 [hp_C]/1 mL; ORNITHOGALUM UMBELLATUM FLOWERING TOP 30 [hp_C]/1 mL; PRUNUS CERASIFERA FLOWER 30 [hp_C]/1 mL
INACTIVE INGREDIENTS: WATER; ALCOHOL

DRUG FACTS:

ACTIVE INGREDIENTS:

Aralia Quinquefolia 3X, Clematis Vitalba, Flos 30C, 200C, Cobaltum Metallicum 12X, Cuprum Metallicum 12X, Gelsemium Sempervirens 12X, Ginkgo Biloba 3X, Helianthemum Nummularium, Flos 30C, 200C, Hydrocotyle Asiatica 3X, Impatiens Glandulifera, Flos 30C, 200C, Iodium 12X, Lomatium Dissectum 3X, Ornithogalum Umbellatum, Flos 30C, 200C, Prunus Cerasifera, Flos 30C, 200C, Vanadium Metallicum 12X.

PURPOSE:

Aralia Quinquefolia - Stress, Clematis Vitalba, Flos – Mood Swings, Cobaltum Metallicum – Sleep Problems, Cuprum Metallicum - Nausea, Gelsemium Sempervirens - Vomiting, Ginkgo Biloba – Head Pain, Helianthemum Nummularium, Flos - Stress, Hydrocotyle Asiatica – Poor Digestion, Impatiens Glandulifera, Flos – Mood Swings, Iodium – Sleep Problems, Lomatium Dissectum - Nausea, Ornithogalum Umbellatum, Flos - Vomiting, Prunus Cerasifera, Flos – Poor Digestion, Vanadium Metallicum – Head Pain

USES:

• For the temporary relief of symptoms including:

• stress • mood swings • sleep problems • nausea

• vomiting • head pain • poor digestion

These statements are based upon homeopathic principles. They have not been reviewed by the Food and Drug Administration.

WARNINGS:

If pregnant of breast-feeding, ask a health professional before use.

Keep out of reach of children. In case of overdose, contact a physician or Poison Control Center right away.

Tamper Evident: Sealed for your protection. Do not use if seal is broken or missing.

KEEP OUT OF REACH OF CHILDREN.

In case of overdose, contact a physician or Poison Control Center right away.

DIRECTIONS:

1-10 drops under the tongue, 3 times a day or as directed by a health professional. Consult a physician for use in children under 12 years of age.

INACTIVE INGREDIENTS:

Demineralized water, 25% ethanol

QUESTIONS:

Dist. By: Deseret Biologicals, Inc.

469 W. Parkland Drive

Sandy, UT 84070

www.desbio.com

800-827-8204

PACKAGE LABEL DISPLAY:

Des Bio

Stress EZ

Homeopathic

NDC 43742-2059-1
1 FL OZ (30 ml)